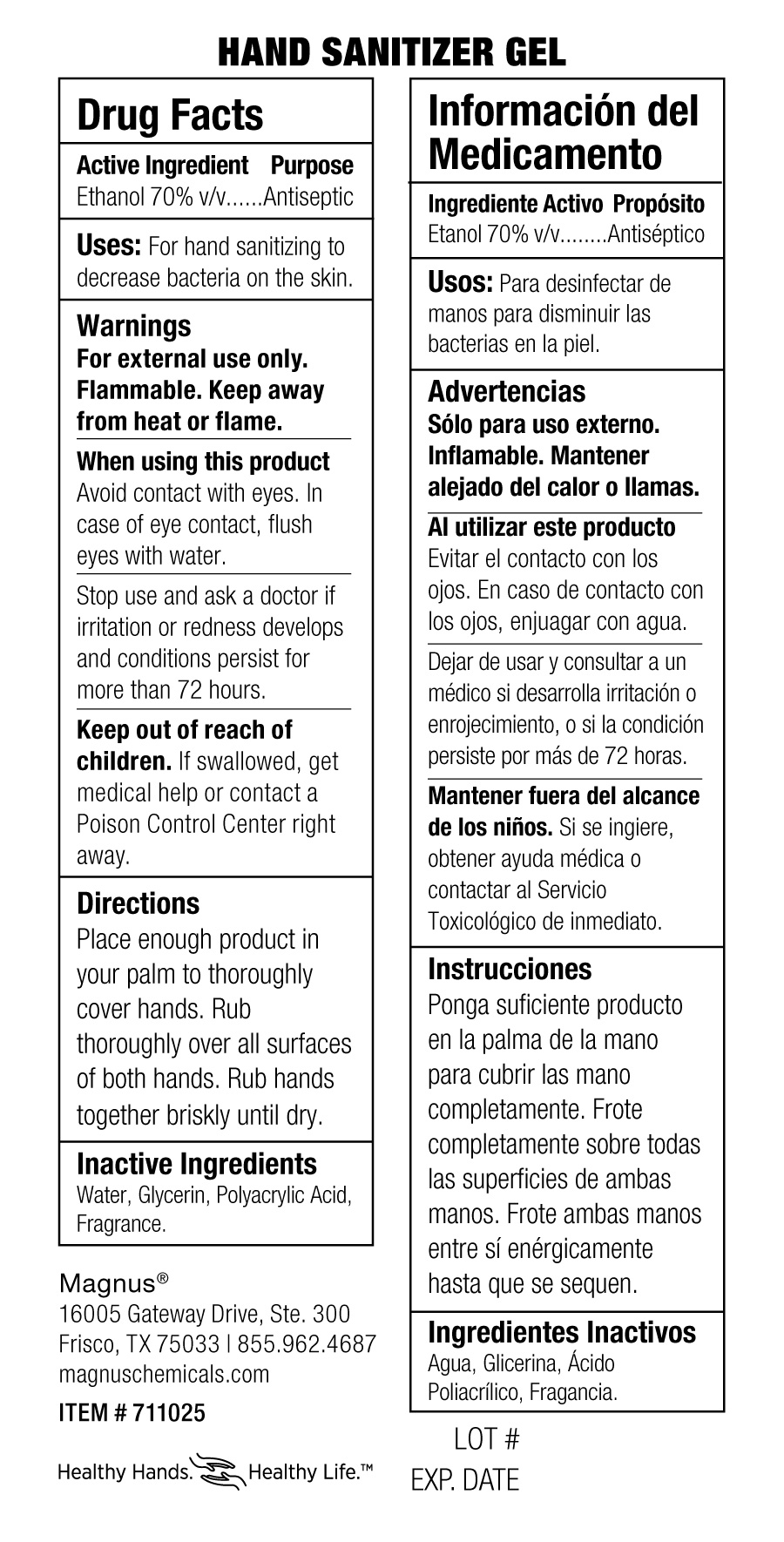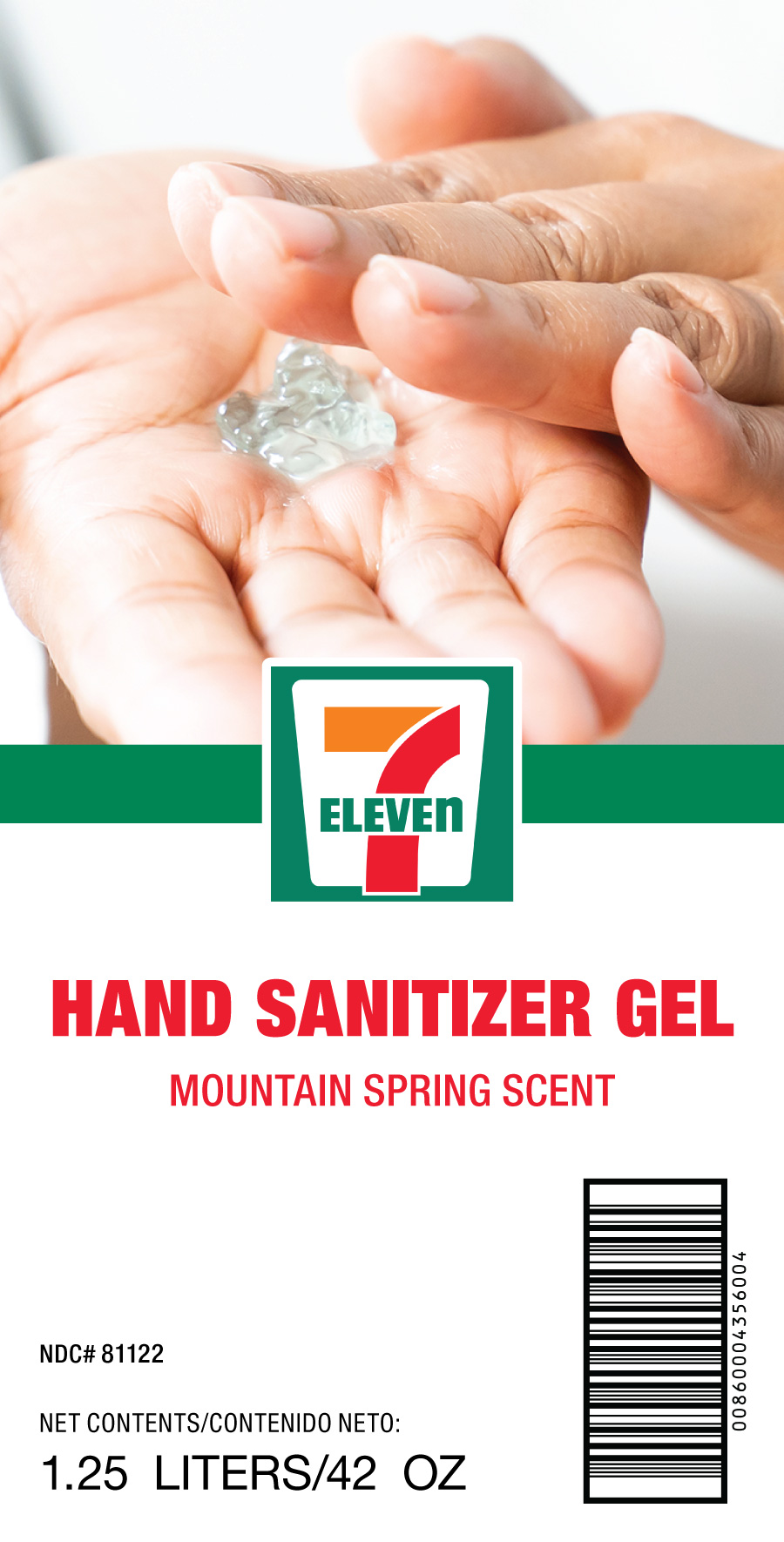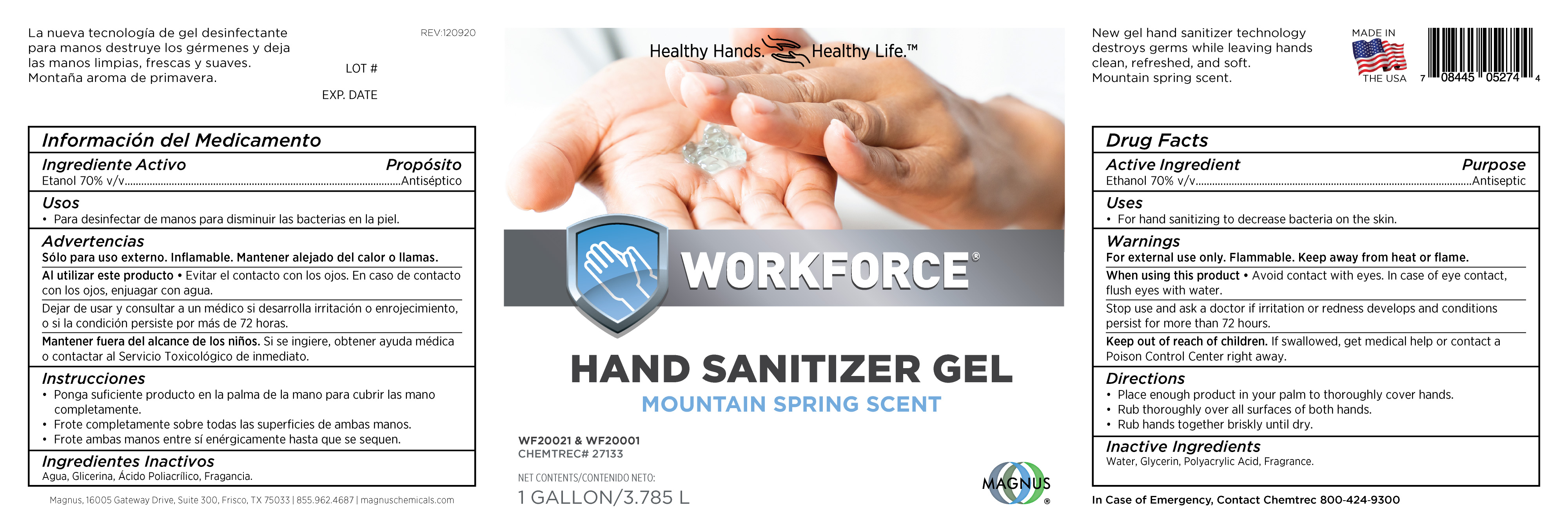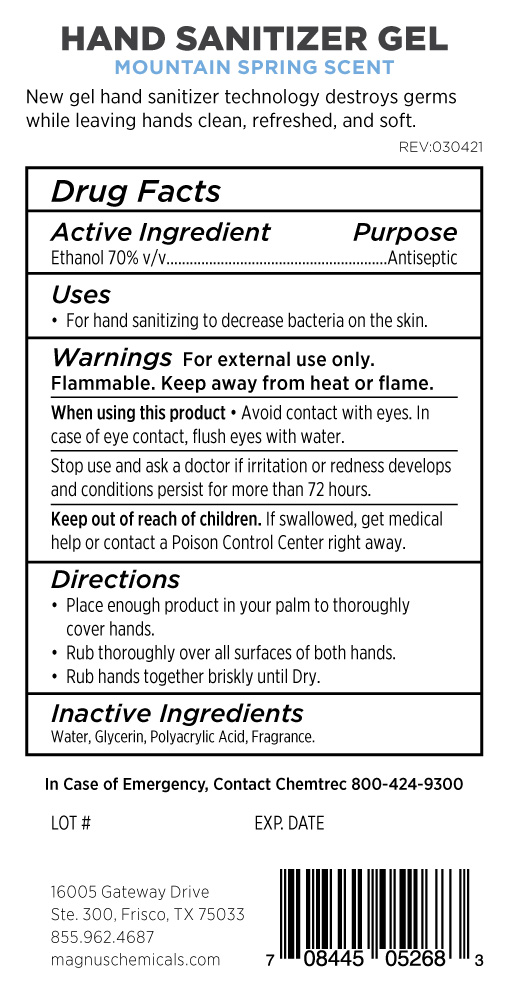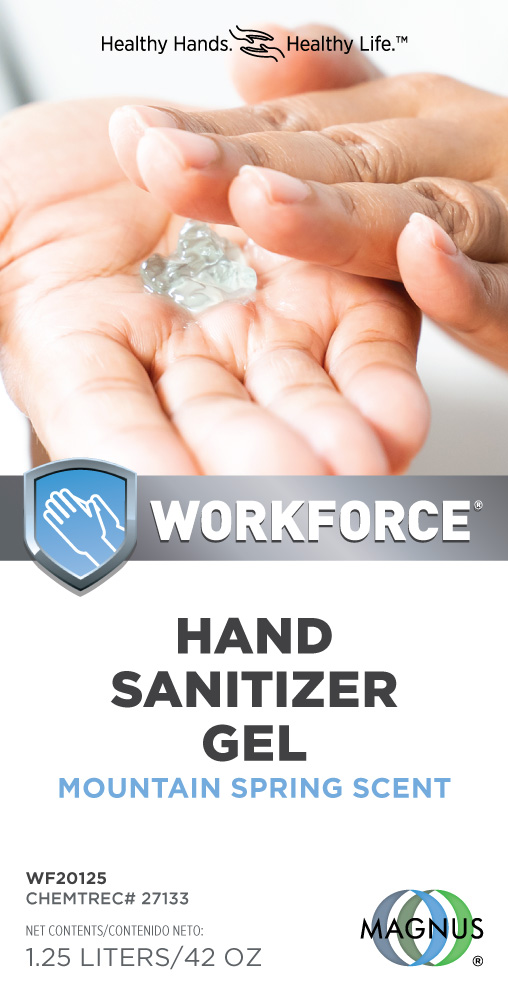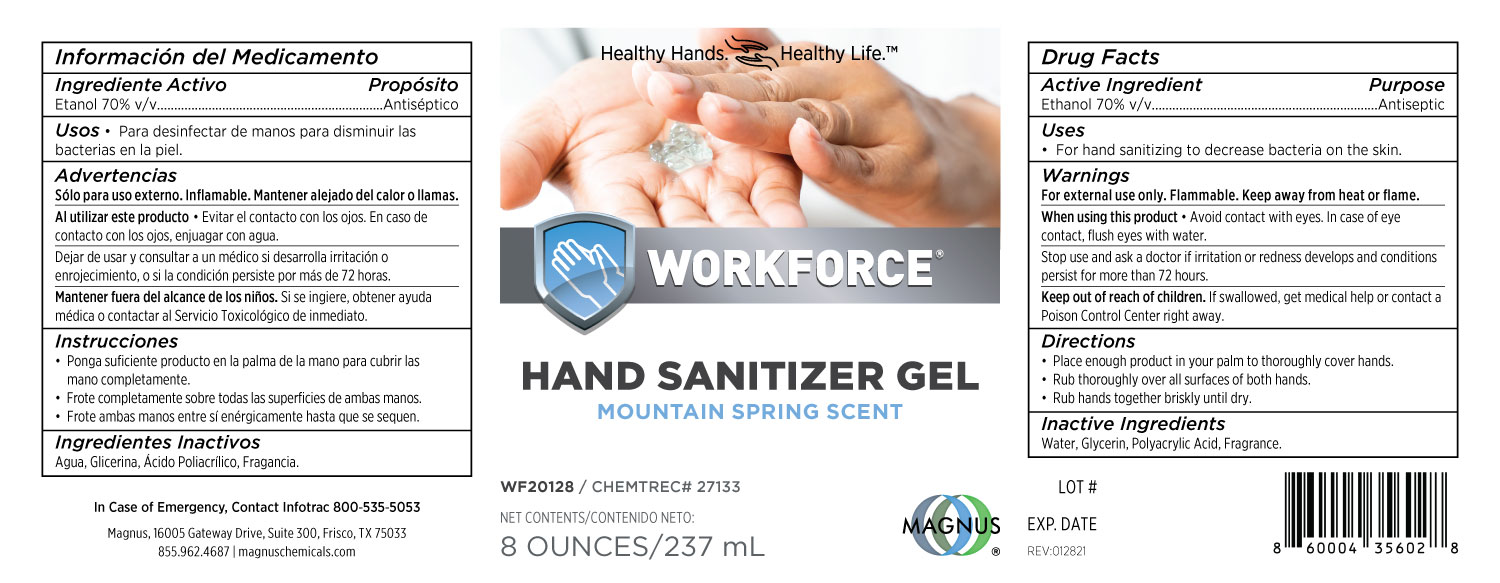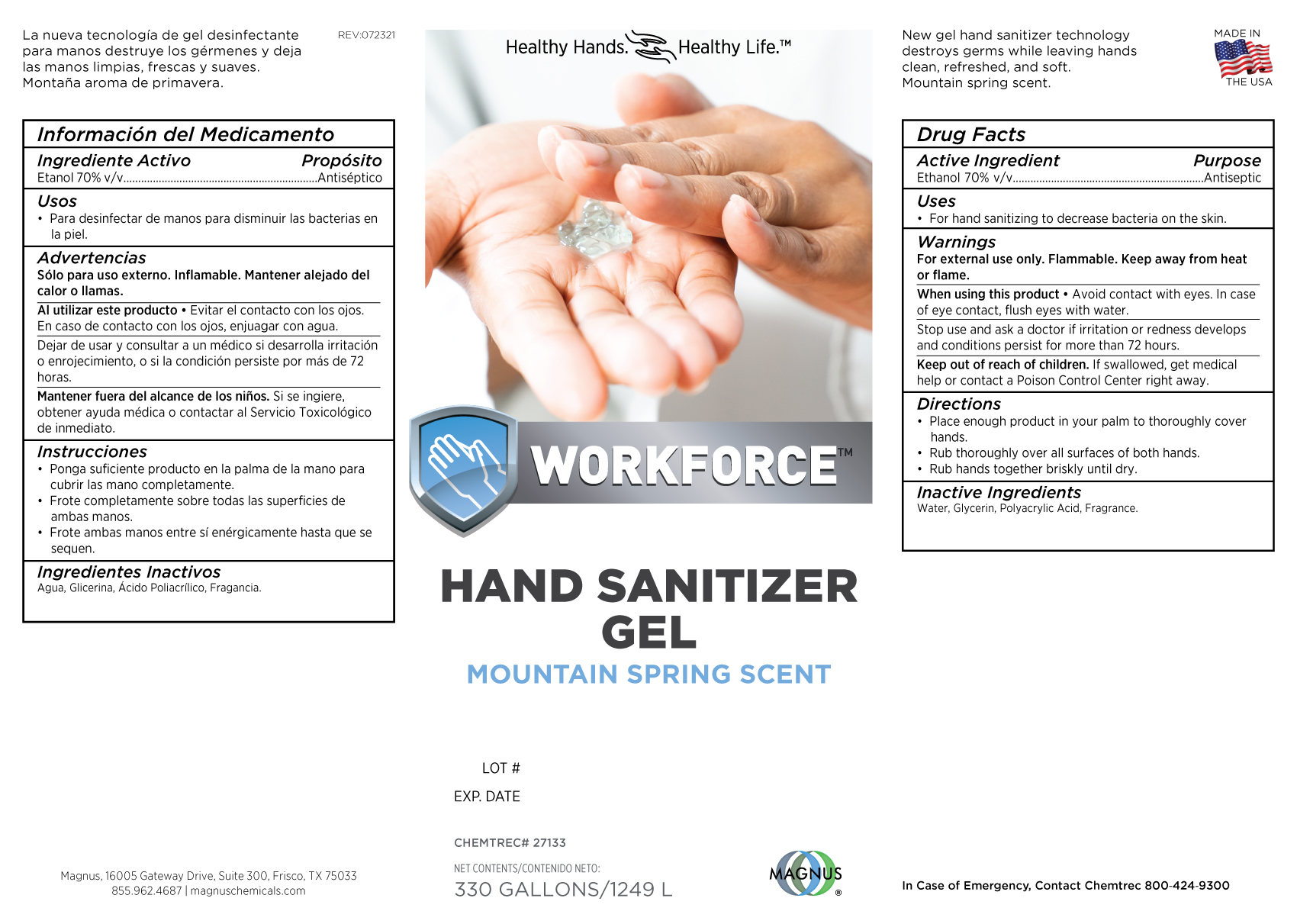 DRUG LABEL: WORKFORCE HAND SANITIZER
NDC: 81122-233 | Form: GEL
Manufacturer: Magnus Procurement & Logistics Solution, Inc.
Category: otc | Type: HUMAN OTC DRUG LABEL
Date: 20220919

ACTIVE INGREDIENTS: ALCOHOL 70 mL/100 mL
INACTIVE INGREDIENTS: WATER; FRAGRANCE CLEAN ORC0600327; METHACRYLIC ACID AND ETHYL ACRYLATE COPOLYMER; GLYCERIN

27133 Magnus (Dye Free)

Active Ingredient Purpose

Ethanol 70% v/v........Antiseptic

Warnings

For external use only. Flammable. Keep away from heat or flame.

When using this product

Avoid contact with eyes. In case of eye contact, flush eyes with water.

Keep out of reach of children. If swallowed, get medical help or contact a Poison Control Center right away.

Inactive Ingredients

Water, Glycerin, Polyacrylic Acid, Frangrance.

PURPOSE

Antiseptic, Hand Sanitizer

Stop use and ask a doctor if irritation or redness develops and conditions persist for more than 72 hours.

INDICATIONS AND USAGE

Uses: For hand sanitizing to decrease bacteria on the skin.

Directions

Place enough product in your palm to thoroughly cover hands. Rub thoroughly over all surfaces of both hands. Rub hands together briskly until dry.

PACKAGE LABEL

1.25L Front 81122-133-25

PACKAGE LABEL

1.25L Back 81122-133-25

PACKAGE LABEL

27133 81122-233-01